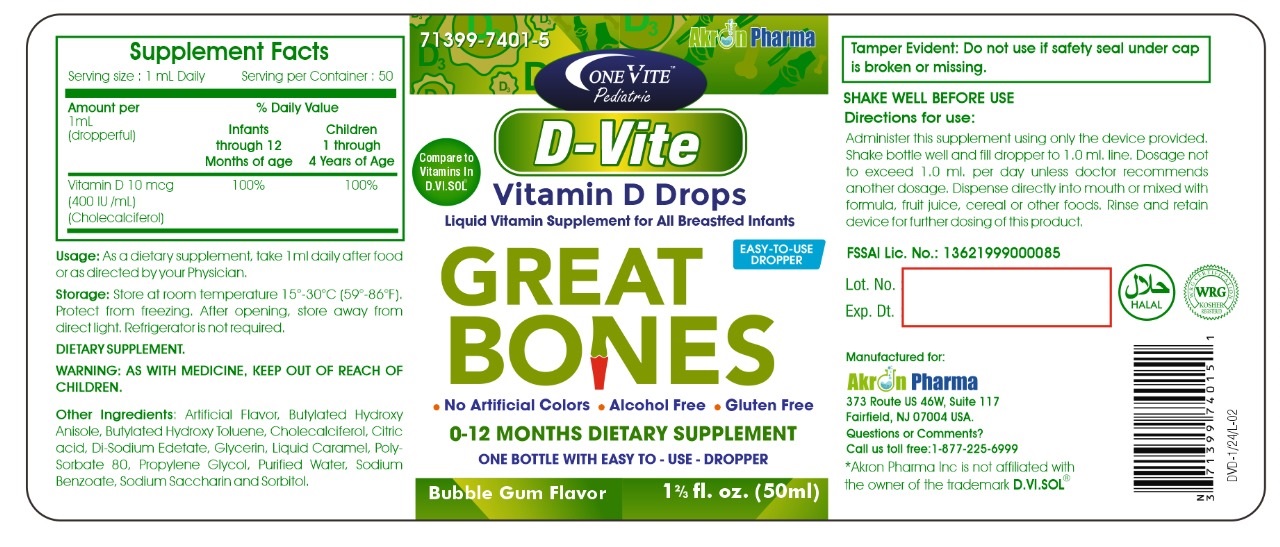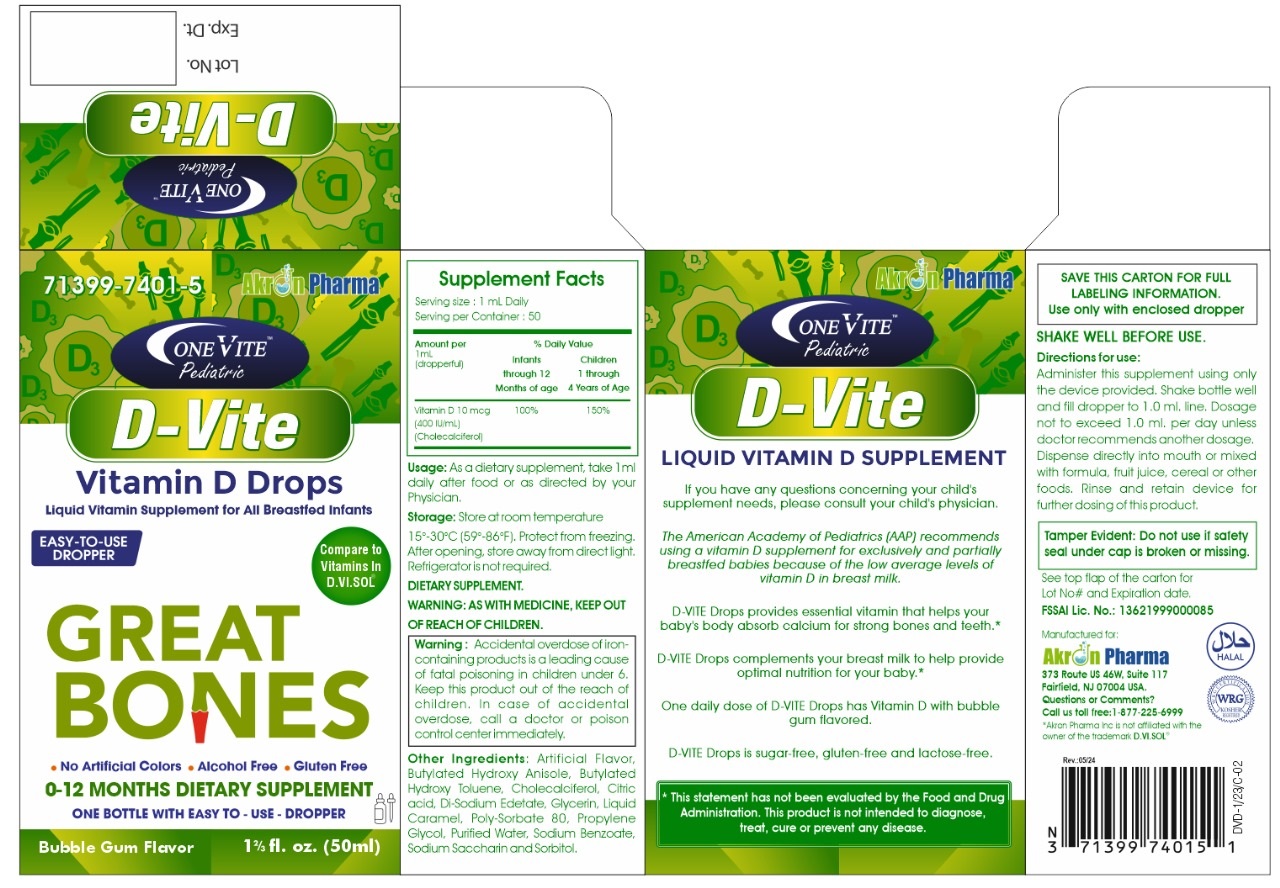 DRUG LABEL: D-Vite Pediatric Oral Liquid
NDC: 71399-7401 | Form: SOLUTION
Manufacturer: Akron Pharma
Category: other | Type: DIETARY SUPPLEMENT
Date: 20240523

ACTIVE INGREDIENTS: CHOLECALCIFEROL 400 [iU]/1 mL
INACTIVE INGREDIENTS: BUTYLATED HYDROXYANISOLE; BUTYLATED HYDROXYTOLUENE; ANHYDROUS CITRIC ACID; EDETATE DISODIUM; GLYCERIN; CARAMEL; POLYSORBATE 80; PROPYLENE GLYCOL; WATER; SODIUM BENZOATE; SACCHARIN SODIUM; SORBITOL

OneVite Pediatric D-VITE
Vitamin D Drops
Liquid Vitamin Supplement for All Breastfed Infants

STATEMENT OF IDENTITY

Supplement Facts

Serving Size: 1 mL Daily

Serving per Container:50

Amount Per mL (dropperful) % Daily Value

Infants through 12 months of age Children 1 through 4 years of age

400 IU/mL

(CHOLECALCIFEROL) 100% 150%

HEALTH CLAIM

D-VITE Drops provides essential vitamin that helps your baby's body absorb calcium for strong bones and teeth.*

D-VITE Drops complements your breast milk to help provide optimal nutrition for your baby. *

* This statment has not been evaluated by the Food and Drug Administration. This product is not intended to diagnose, treat, cure or prevent any disease.

SAFE HANDLING WARNING

Storage: Store at room temperature 15º -30ºC(59º -86ºF). Protect from freezing. After opening, store away from direct light. Refrigerator is not required.

WARNINGS

WARNING: As with medicine, Keep out of reach of children.

PRECAUTIONS

SHAKE WELL BEFORE USE.

DOSAGE AND ADMINISTRATION

Directions for use:

Administer this supplement using only the device provided Shake bottle well and fill dropper to 1.0 ml. line. Dosage not to exceed 1.0 ml. per day unless doctor recommends another dosage. Dispense directly into mouth or mixed with formula, fruit juice, cereal, or other foods. Rinse and retain device for further dosing of this product.